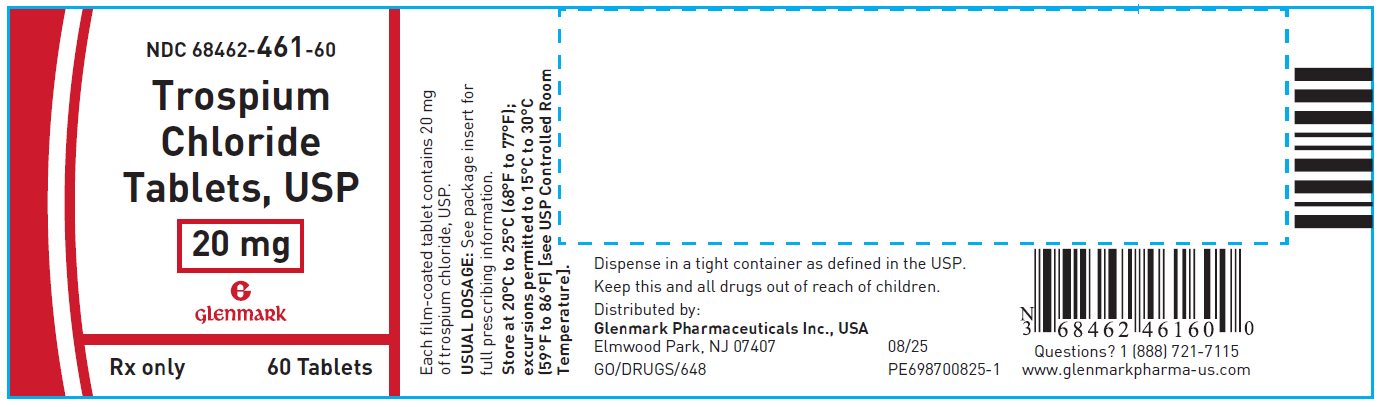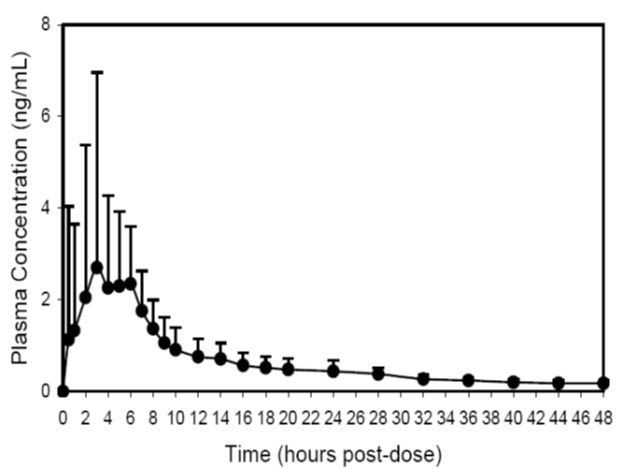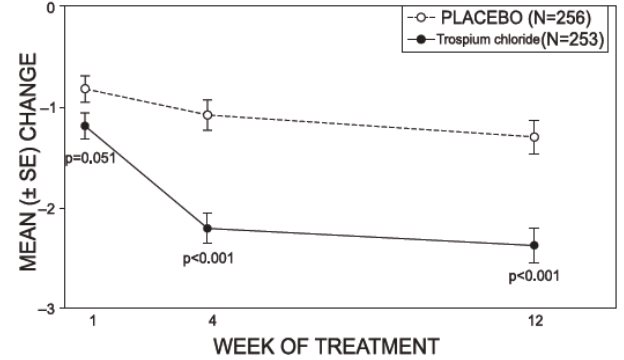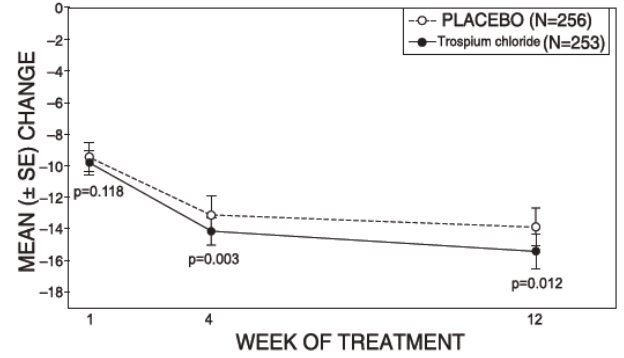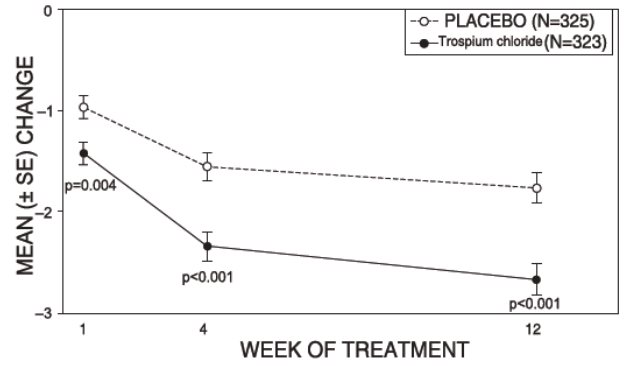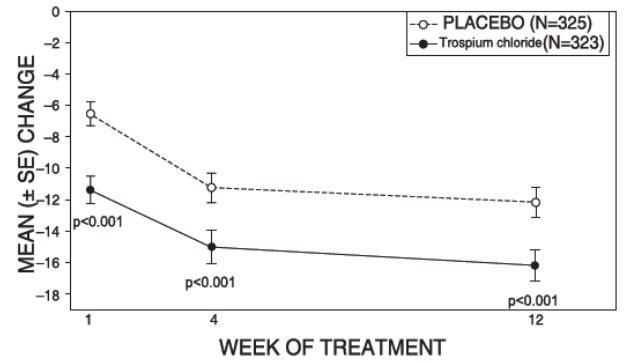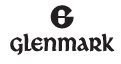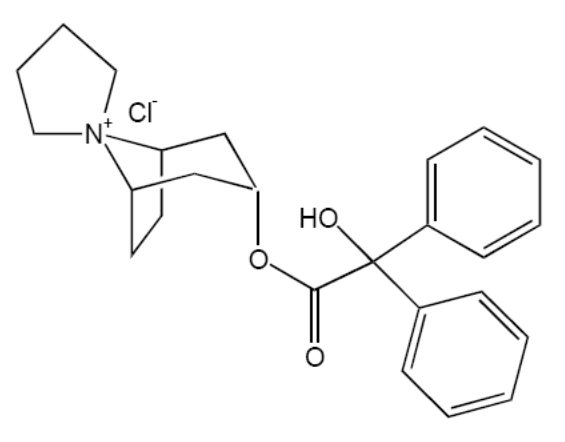 DRUG LABEL: Trospium Chloride
NDC: 68462-461 | Form: TABLET, FILM COATED
Manufacturer: Glenmark Pharmaceuticals Inc., USA
Category: prescription | Type: HUMAN PRESCRIPTION DRUG LABEL
Date: 20251230

ACTIVE INGREDIENTS: TROSPIUM CHLORIDE 20 mg/1 1
INACTIVE INGREDIENTS: MICROCRYSTALLINE CELLULOSE; LACTOSE MONOHYDRATE; STARCH, CORN; POVIDONE, UNSPECIFIED; CROSCARMELLOSE SODIUM; SILICON DIOXIDE; MAGNESIUM STEARATE; TITANIUM DIOXIDE; POLYETHYLENE GLYCOL 400; HYPROMELLOSE, UNSPECIFIED; FERRIC OXIDE YELLOW; FERRIC OXIDE RED

HIGHLIGHTS OF PRESCRIBING INFORMATION

These highlights do not include all the information needed to use TROSPIUM CHLORIDE TABLETS safely and effectively. See full prescribing information for TROSPIUM CHLORIDE TABLETS.
TROSPIUM CHLORIDE tablets, for oral use
Initial U.S. Approval: 2004

1 INDICATIONS AND USAGE

Trospium chloride tablets are a muscarinic antagonist indicated for the treatment of overactive bladder (OAB) with symptoms of urge urinary incontinence, urgency, and urinary frequency. (1)

2 DOSAGE AND ADMINISTRATION

- The recommended dose of trospium chloride tablets is one 20 mg tablet twice daily. Trospium chloride tablets should be dosed with water on an empty stomach, at least one hour before a meal. (2)
- For patients with severe renal impairment (creatinine clearance less than 30 mL/min), the recommended dose is 20 mg once daily at bedtime. (2)
- In geriatric patients greater than or equal to 75 years of age, dose may be titrated down to 20 mg once daily based upon tolerability. (2)

3 DOSAGE FORMS AND STRENGTHS

20 mg tablets. (3)

4 CONTRAINDICATIONS

Trospium chloride is contraindicated in

- patients with urinary retention, gastric retention, or uncontrolled narrow-angle glaucoma, and in patients who are at risk for these conditions (4)
- patients with known hypersensitivity (4)

5 WARNINGS AND PRECAUTIONS

- Trospium chloride should be administered with caution to patients with clinically significant bladder outflow obstruction or gastrointestinal obstructive disorders due to risk of urinary or gastric retention. (5.1, 5.3)
- Angioedema of the face, lips, tongue and/or larynx has been reported with trospium chloride. (5.2)
- In patients with controlled narrow angle glaucoma trospium chloride should be used only with careful monitoring. (5.4)
- Central Nervous System Effects: Somnolence has been reported with trospium chloride. Advise patients not to drive or operate heavy machinery until they know how trospium chloride affects them (5.5).
- Trospium is substantially excreted by the kidney. The effects of moderate renal impairment on systemic exposure are not known but systemic exposure is likely increased. Therefore, the risk of anticholinergic adverse reactions is expected to be greater in patients with moderate renal impairment. (5.6)

6 ADVERSE REACTIONS

The most common adverse reactions (greater than or equal to 1%) with trospium chloride are dry mouth (20.1%), constipation (9.6%), and headache (4.2%). (6.1)

To report SUSPECTED ADVERSE REACTIONS, contact Glenmark Pharmaceuticals Inc., USA at 1 (888) 721-7115 or FDA at 1-800-FDA-1088 or www.fda.gov/medwatch.

7 DRUG INTERACTIONS

- Concomitant use with digoxin did not affect the pharmacokinetics of either drug. (7.1)
- Some drugs which are actively secreted by the kidney may interact with trospium chloride by competing for renal tubular secretion. (7.2)
- Concomitant use with metformin immediate release tablets reduced exposure and peak concentration of trospium. (7.4)

8 USE IN SPECIFIC POPULATIONS

- The safety and effectiveness of trospium chloride in pediatric patients have not been established. (8.4)

FULL PRESCRIBING INFORMATION

1 INDICATIONS AND USAGE

Trospium chloride tablets are a muscarinic antagonist indicated for the treatment of overactive bladder (OAB) with symptoms of urge urinary incontinence, urgency, and urinary frequency.

2 DOSAGE AND ADMINISTRATION

The recommended dose is 20 mg twice daily. Trospium chloride tablets should be dosed at least one hour before meals or given on an empty stomach.

Dosage modification is recommended in the following patient populations:

- For patients with severe renal impairment (creatinine clearance less than 30 mL/min), the recommended dose is 20 mg once daily at bedtime [see Warnings and Precautions (5.5), Use in Specific Populations (8.6), and Clinical Pharmacology (12.3)].
- In geriatric patients greater than or equal to 75 years of age, dose may be titrated down to 20 mg once daily based upon tolerability [see Use in Specific Populations (8.5)].

3 DOSAGE FORMS AND STRENGTHS

Trospium Chloride Tablets, USP are supplied as 20 mg tablets (brownish yellow, round, biconvex film-coated tablets, debossed with ‘L’ on one side and ‘1’ on the other side).

4 CONTRAINDICATIONS

Trospium chloride is contraindicated in patients with:

- urinary retention
- gastric retention
- uncontrolled narrow-angle glaucoma.
- known hypersensitivity to the drug or its ingredients. Angioedema, rash and anaphylactic reaction have been reported.

5 WARNINGS AND PRECAUTIONS

5.1 Risk of Urinary Retention

Trospium chloride should be administered with caution to patients with clinically significant bladder outflow obstruction because of the risk of urinary retention [see Contraindications (4)].

5.2 Angioedema

Angioedema of the face, lips, tongue, and/or larynx has been reported with trospium chloride, the active ingredient in trospium chloride. In one case, angioedema occurred after the first dose of trospium chloride. Angioedema associated with upper airway swelling may be life threatening. If involvement of the tongue, hypopharynx, or larynx occurs, trospium chloride should be promptly discontinued and appropriate therapy and/or measures necessary to ensure a patent airway should be promptly provided.

5.3 Decreased Gastrointestinal Motility

Trospium chloride should be administered with caution to patients with gastrointestinal obstructive disorders because of the risk of gastric retention [see Contraindications (4)]. Trospium chloride, like other antimuscarinic agents, may decrease gastrointestinal motility and should be used with caution in patients with conditions such as ulcerative colitis, intestinal atony and myasthenia gravis.

5.4 Controlled Narrow-angle Glaucoma

In patients being treated for narrow-angle glaucoma, trospium chloride should only be used if the potential benefits outweigh the risks and in that circumstance only with careful monitoring [see Contraindications (4)].

5.5 Central Nervous System Effects

Trospium chloride is associated with anticholinergic central nervous system (CNS) effects [see Adverse Reactions (6.2)]. A variety of CNS anticholinergic effects have been reported, including dizziness, confusion, hallucinations and somnolence. Patients should be monitored for signs of anticholinergic CNS effects, particularly after beginning treatment or increasing the dose. Advise patients not to drive or operate heavy machinery until they know how trospium chloride affects them. If a patient experiences anticholinergic CNS effects, dose reduction or drug discontinuation should be considered.

5.6 Anticholinergic Adverse Reactions in Patients with Moderate Renal Impairment

Trospium is substantially excreted by the kidney. The effects of moderate renal impairment on systemic exposure are not known but systemic exposure is likely increased. Therefore, anticholinergic adverse reactions (including dry mouth, constipation, dyspepsia, urinary tract infection, and urinary retention) are expected to be greater in patients with moderate renal impairment [see Dosage and Administration (2), and Use in Specific Populations (8.6)].

6 ADVERSE REACTIONS

6.1 Clinical Trials Experience

Because clinical trials are conducted under widely varying conditions, the adverse reaction rates observed in the clinical trials of a drug cannot be directly compared to rates in the clinical trials of another drug and may not reflect the rates observed in clinical practice.

The safety of trospium chloride was evaluated in controlled clinical trials in a total of 2975 patients, who were treated with trospium chloride (N=1673), placebo (N=1056) or active control medications (N=246). Of this total, 1181 patients participated in two, 12-week, U.S., efficacy and safety studies and a 9-month open-label extension. Of this total, 591 patients received trospium chloride 20 mg twice daily. In all controlled trials combined, 232 and 208 patients received treatment with trospium chloride for at least 24 and 52 weeks, respectively.

In all placebo-controlled trials combined, the incidence of serious adverse events was 2.9% among patients receiving trospium chloride 20 mg twice daily and 1.5% among patients receiving placebo. Table 1 lists adverse reactions from the combined 12-week U.S. safety and efficacy trials were reported by at least 1% of patients, and were reported more frequently in the trospium chloride group than in the placebo group.

The two most common adverse reactions reported by patients receiving trospium chloride 20 mg twice daily were dry mouth and constipation. The single most frequently reported adverse reaction for trospium chloride, dry mouth, occurred in 20.1% of trospium chloride treated patients and 5.8% of patients receiving placebo. In the two U.S. studies, dry mouth led to discontinuation in 1.9% of patients treated with trospium chloride 20 mg twice daily. For the patients who reported dry mouth, most had their first occurrence of the event within the first month of treatment.

Table 1. Incidence (%) of adverse reactions with trospium chloride, reported in greater than or equal to 1% of all patients treated with trospium chloride and more frequent with trospium chloride (20 mg twice daily) than placebo in Studies 1 and 2 combined

Adverse Reaction | Placebo; (N=590) | Trospium Chloride 20 mg; twice daily; (N=591)
Gastrointestinal Disorders
Dry mouth | 34 (5.8) | 119 (20.1)
Constipation | 27 (4.6) | 57 (9.6)
Abdominal pain upper | 7 (1.2) | 9 (1.5)
Constipation aggravated | 5 (0.8) | 8 (1.4)
Dyspepsia | 2 (0.3) | 7 (1.2)
Flatulence | 5 (0.8) | 7 (1.2)
Nervous System Disorders
Headache | 12 (2) | 25 (4.2)
General Disorders
Fatigue | 8 (1.4) | 11 (1.9)
Renal and Urinary Disorders
Urinary retention | 2 (0.3) | 7 (1.2)
Eye Disorders
Dry eyes | 2 (0.3) | 7 (1.2)

Other adverse reactions from the U.S., placebo-controlled trials, occurring in greater than or equal to 0.5% and less than 1% of trospium chloride treated patients, and more common with trospium chloride than placebo are: tachycardia, vision blurred, abdominal distension, vomiting, dysgeusia, dry throat, and dry skin.

During controlled clinical studies, one adverse reaction of angioneurotic edema was reported.

6.2 Post-marketing Experience

The following adverse reactions have been identified during post-approval use of trospium chloride. Because these reactions are reported voluntarily from a population of uncertain size, it is not always possible to reliably estimate their frequency or establish a causal relationship to drug exposure.

Gastrointestinal – gastritis; Cardiovascular – palpitations, supraventricular tachycardia, chest pain, syncope, “hypertensive crisis”; Immunological – Stevens-Johnson syndrome, anaphylactic reaction, angioedema; Nervous System – dizziness, confusion, vision abnormal, hallucinations, somnolence and delirium; Musculoskeletal – rhabdomyolysis; General – rash.

7 DRUG INTERACTIONS

7.1 Digoxin

Concomitant use of trospium chloride and digoxin did not affect the pharmacokinetics of either drug [see Clinical Pharmacology (12.3)].

7.2 Drugs Eliminated by Active Tubular Secretion

Although demonstrated in a drug-drug interaction study not to affect the pharmacokinetics of digoxin, trospium chloride has the potential for pharmacokinetic interactions with other drugs that are eliminated by active tubular secretion (e.g., procainamide, pancuronium, morphine, vancomycin, and tenofovir). Coadministration of trospium chloride with these drugs may increase the serum concentration of trospium chloride and/or the coadministered drug due to competition for this elimination pathway. Careful patient monitoring is recommended in patients receiving such drugs [see Clinical Pharmacology (12.3)].

7.3 Antimuscarinic Agents

The concomitant use of trospium chloride with other antimuscarinic agents that produce dry mouth, constipation, and other anticholinergic pharmacological effects may increase the frequency and/or severity of such effects. Trospium chloride may potentially alter the absorption of some concomitantly administered drugs due to anticholinergic effects on gastrointestinal motility.

7.4 Metformin

Co-administration of 500 mg metformin immediate release tablets twice daily with trospium chloride 60 mg extended release reduced the steady-state systemic exposure of trospium by approximately 29% for mean AUC0 to 24 and by 34% for mean Cmax [see Clinical Pharmacology (12.3)].

8 USE IN SPECIFIC POPULATIONS

8.1 Pregnancy

Teratogenic Effects

Pregnancy Category C:

There are no adequate and well-controlled studies of trospium chloride in pregnant women. Trospium chloride should be used during pregnancy only if the potential benefit to the patient outweighs the risk to the patient and fetus. Women who become pregnant during trospium chloride treatment are encouraged to contact their physician.

Risk Summary

Based on animal data, trospium chloride is predicted to have a low probability of increased risk of adverse developmental outcomes, above background risk. Adverse developmental findings were not observed to correlate with dose in rats or in rabbits. No increased risk above background was observed in rats and rabbits treated at an exposure approximately equivalent to the maximal recommended human dose (MRHD) of 40 mg.

Animal Data

In a rat embryo/fetal development study, pregnant rats received doses of trospium chloride up to 200 mg/kg/day, from implantation to closure of the fetal hard palate, with maternal systemic exposures corresponding to approximately nine times the exposure of women treated at the MRHD of 40 mg, based on AUC. No malformations or fetal toxicity were observed.

The offspring of female rats exposed orally, pre- and post-natally, to trospium chloride up to 200 mg/kg/day showed no increased developmental toxicity over background in surviving pups. However, maternal toxicity (death, irregular breathing, increased excitability) was observed at 200 mg/kg/day. A no-effect level for maternal and pup toxicity (survival to Day 4) was 20 mg/kg/day, an exposure approximately equivalent to the maximal recommended human dose (MRHD) of 40 mg.

In a rabbit embryo/fetal development study, pregnant rabbits received doses of trospium chloride up to 200 mg/kg/day, from implantation to closure of the fetal hard palate. At 200 mg/kg/day, maternal systemic exposures corresponded to approximately 16 times the exposure of women treated at the MRHD of 40 mg, based on AUC. However, one fetus in each of the three treated dose groups (0.3 to 16 times exposures at the MRHD) demonstrated multiple malformations, including umbilical hernia and skeletal malformations. A maternal no-effect level was set at 20 mg/kg/day, at an exposure approximately equivalent to the maximal recommended human dose (MRHD) of 40 mg, due to clinical signs (reduced feces, hunched posture, diarrhea) observed in a pharmacokinetic study at 200 mg/kg/day.

8.2 Labor and Delivery

The effect of trospium chloride tablets on labor and delivery is unknown.

8.3 Nursing Mothers

Trospium chloride (2 mg/kg orally and 50 mcg/kg intravenously) was excreted, to a limited extent (less than 1%), into the milk of lactating rats (primarily as parent compound). It is not known whether this drug is excreted in human milk. Because many drugs are excreted in human milk, trospium chloride should be used during lactation only if the potential benefit justifies the potential risk to the newborn.

8.4 Pediatric Use

The safety and effectiveness of trospium chloride in pediatric patients have not been established.

8.5 Geriatric Use

Of the 591 patients with overactive bladder who received treatment with trospium chloride in the two U.S., placebo-controlled, efficacy and safety studies, 249 patients (42%) were 65 years of age and older. Eighty-eight trospium chloride treated patients (15%) were greater than or equal to 75 years of age.

In these 2 studies, the incidence of commonly reported anticholinergic adverse reactions in patients treated with trospium chloride (including dry mouth, constipation, dyspepsia, urinary tract infection, and urinary retention) was higher in patients 75 years of age and older as compared to younger patients. This effect may be related to an enhanced sensitivity to anticholinergic agents in this patient population [see Clinical Pharmacology (12.3)]. Therefore, based upon tolerability, the dose frequency of trospium chloride may be reduced to 20 mg once daily in patients 75 years of age and older.

8.6 Renal Impairment

Severe renal impairment (creatinine clearance less than 30 mL/minute) significantly altered the disposition of trospium chloride. A 4.2-fold and 1.8-fold increase in mean AUC(0 to ∞) and Cmax, respectively, and the appearance of an additional elimination phase with a long half-life (~33 hr) were detected in patients with severe renal impairment compared with nearly age-matched subjects with creatinine clearance equal to or higher than 80 mL/min. The different pharmacokinetic behavior of trospium chloride in patients with severe renal impairment necessitates adjustment of dosage frequency [see Dosage and Administration (2)]. The pharmacokinetics of trospium have not been studied in patients with creatinine clearance ranging from 30 to 80 mL/min.

Trospium is known to be substantially excreted by the kidney, and the risk of adverse reactions may be greater in patients with impaired renal function.

8.7 Hepatic Impairment

There is no information regarding the effect of severe hepatic impairment on exposure to trospium chloride. In a study of patients with mild and with moderate hepatic impairment, given 40 mg of immediate-release trospium chloride, mean Cmax increased 12% and 63%, respectively, and mean AUC(0 to ∞) decreased 5% and 15%, respectively, compared to healthy subjects. The clinical significance of these findings is unknown. Caution should be used when administering trospium chloride to patients with moderate and severe hepatic impairment.

10 OVERDOSAGE

Overdosage with antimuscarinic agents, including trospium chloride, can result in severe antimuscarinic effects. Supportive treatment should be provided according to symptoms. In the event of overdosage, electrocardiographic monitoring is recommended.

A 7-month-old baby experienced tachycardia and mydriasis after administration of a single dose of trospium 10 mg given by a sibling. The baby’s weight was reported as 5 kg. Following admission into the hospital and about 1 hour after ingestion of the trospium, medicinal charcoal was administered for detoxification. While hospitalized, the baby experienced mydriasis and tachycardia up to 230 beats per minute. Therapeutic intervention was not deemed necessary. The baby was discharged as completely recovered the following day.

11 DESCRIPTION

Trospium chloride, USP is a quaternary ammonium compound with the chemical name of Spiro [8-azoniabicyclo[3.2.1]octane-8,1'-pyrrolidinium], 3-[(hydroxydiphenylacetyl)oxy]-, chloride, (1R, 3r, 5S). The empirical formula of trospium chloride, USP is C25H30ClNO3 and its molecular weight is 427.96 g/mol. The structural formula of trospium chloride, USP is represented below:

Trospium chloride, USP is a white or almost white, crystalline powder. It is very soluble in water, freely soluble in methanol, practically insoluble in methylene chloride.

Each Trospium Chloride Tablet, USP contains 20 mg of trospium chloride, USP, a muscarinic antagonist, for oral administration. Each tablet also contains the following inactive ingredients: microcrystalline cellulose, lactose monohydrate, corn starch, povidone, croscarmellose sodium, colloidal silicon dioxide, magnesium stearate, titanium dioxide, polyethylene glycol 400, hypromellose, yellow iron oxide and red iron oxide.

12 CLINICAL PHARMACOLOGY

12.1 Mechanism of Action

Trospium chloride is a muscarinic antagonist.

Trospium chloride antagonizes the effect of acetylcholine on muscarinic receptors in cholinergically innervated organs including the bladder. Its parasympatholytic action reduces the tonus of smooth muscle in the bladder.

Receptor assays showed that trospium chloride has negligible affinity for nicotinic receptors as compared to muscarinic receptors at concentrations obtained from therapeutic doses.

12.2 Pharmacodynamics

Placebo-controlled studies employing urodynamic variables were conducted in patients with conditions characterized by involuntary detrusor contractions. The results demonstrate that trospium chlorideincreases maximum cystometric bladder capacity and volume at first detrusor contraction.

Electrophysiology

The effect of 20 mg twice daily and up to 100 mg twice daily trospium chloride on QT interval was evaluated in a single-blind, randomized, placebo and active (moxifloxacin 400 mg once daily) controlled 5 day parallel trial in 170 male and female healthy volunteer subjects aged 18 to 45 years. The QT interval was measured over a 24-hour period at steady state. The 100 mg twice daily dose of trospium chloride was chosen because this achieves the Cmax expected in severe renal impairment. Trospium chloride was not associated with an increase in individual corrected (QTcI) or Fridericia corrected (QTcF) QT interval at any time during steady state measurement, while moxifloxacin was associated with a 6.4 msec increase in QTcF.

In this study, asymptomatic, non-specific T wave inversions were observed more often in subjects receiving trospium chloride than in subjects receiving moxifloxacin or placebo following five days of treatment. This finding was not observed during routine safety monitoring in 2 other placebo-controlled clinical trials in 591 trospium chloride treated overactive bladder patients [see Clinical Studies (14)]. The clinical significance of T wave inversion in this study is unknown. Trospium chloride is associated with an increase in heart rate that correlates with increasing plasma concentrations. In the study described above, trospium chloride demonstrated a mean increase in heart rate compared to placebo of 9.1 bpm for the 20 mg dose and of 18 bpm for the 100 mg dose. In the two U.S. placebo-controlled trials in patients with overactive bladder, the mean increase in heart rate compared to placebo in Study 1 was observed to be 3 bpm and in Study 2 was 4 bpm.

12.3 Pharmacokinetics

Absorption:

After oral administration, less than 10% of the dose is absorbed. Mean absolute bioavailability of a 20 mg dose is 9.6% (range: 4 to 16.1%). Peak plasma concentrations (Cmax) occur between 5 to 6 hours post-dose. Mean Cmax increases greater than dose-proportionally; a 3-fold and 4-fold increase in Cmax was observed for dose increases from 20 mg to 40 mg and from 20 mg to 60 mg, respectively. AUC exhibits dose linearity for single doses up to 60 mg. Trospium chloride exhibits diurnal variability in exposure with a decrease in Cmax and AUC of up to 59% and 33%, respectively, for evening relative to morning doses.

Effect of Food:

Administration with a high (50%) fat-content meal resulted in reduced absorption, with AUC and Cmax values 70 to 80% lower than those obtained when trospium chloride was administered while fasting. Therefore, it is recommended that trospium chloride should be taken at least one hour prior to meals or on an empty stomach [see Dosage and Administration (2)].

A summary of mean (± standard deviation) pharmacokinetic parameters for a single 20 mg dose of trospium chloride is provided in Table 2.

Table 2. Mean (± SD) Pharmacokinetic Parameter Estimates for a Single 20 mg Trospium Chloride Tablet Dose in Healthy Volunteers

Cmax | AUC0 to ∞ | Tmax | t½
(ng/mL) | (ng/mL•hr) | (hr) | (hr)
3.5 ± 4 | 36.4 ± 21.8 | 5.3 ± 1.2 | 18.3 ± 3.2

The mean plasma concentration-time (+SD) profile for trospium chloride is shown in Figure 1.

Figure 1 -Mean (+SD) Concentration-Time Profile for a Single 20 mg Oral Dose of Trospium Chloride Tablets in Healthy Volunteers

Distribution:

Protein binding ranged from 50 to 85% when concentration levels of trospium chloride (0.5 to 50 ng/mL) were incubated with human serum in vitro.

The ^3H-trospium chloride ratio of plasma to whole blood was 1.6:1. This ratio indicates that the majority of ^3H-trospium chloride is distributed in plasma.

The apparent volume of distribution for a 20 mg oral dose is 395 (± 140) liters.

Metabolism:

The metabolic pathway of trospium in humans has not been fully defined. Of the 10% of the dose absorbed, metabolites account for approximately 40% of the excreted dose following oral administration. The major metabolic pathway is hypothesized as ester hydrolysis with subsequent conjugation of benzylic acid to form azoniaspironortropanol with glucuronic acid. Cytochrome P450 (CYP) is not expected to contribute significantly to the elimination of trospium. Data taken from in vitro human liver microsomes investigating the inhibitory effect of trospium on seven CYP isoenzyme substrates (CYP1A2, 2A6, 2C9, 2C19, 2D6, 2E1, and 3A4) suggest a lack of inhibition at clinically relevant concentrations.

Excretion:

The plasma half-life for trospium chloride following oral administration is approximately 20 hours. After oral administration of an immediate-release formulation of ^14C-trospium chloride, the majority of the dose (85.2%) was recovered in feces and a smaller amount (5.8% of the dose) was recovered in urine; 60% of the radioactivity excreted in urine was unchanged trospium.

The mean renal clearance for trospium (29.07 L/hour) is 4-fold higher than average glomerular filtration rate, indicating that active tubular secretion is a major route of elimination for trospium. There may be competition for elimination with other compounds that are also renally eliminated [see Drug Interactions (7.2)].

Drug Interactions

Digoxin: Concomitant use of 20 mg trospium chloride immediate release twice daily at steady state and a single dose of 0.5 mg digoxin in a crossover study with 40 male and female subjects did not affect the pharmacokinetics of either drug.

Metformin: A drug interaction study was conducted in which trospium chloride extended release 60 mg once daily was coadministered with Glucophage® (metformin hydrochloride) 500 mg twice daily under steady-state conditions in 44 healthy subjects. Co-administration of 500 mg metformin immediate release tablets twice daily reduced the steady-state systemic exposure of trospium by approximately 29% for mean AUC0 to 24 and by 34% for mean Cmax. The effect of decrease in trospium exposure on the efficacy of trospium chloride extended release is unknown. The steady-state pharmacokinetics of metformin were comparable when administered with or without 60 mg trospium chloride extended release once daily under fasted condition. The effect of metformin at higher doses on trospium PK is unknown.

Specific Populations

Age: Age did not appear to significantly affect the pharmacokinetics of trospium chloride, however, increased anticholinergic side effects unrelated to drug exposure were observed in patients greater than or equal to 75 years of age [see Use in Specific Populations (8.5)].

Pediatric: The pharmacokinetics of trospium chloride were not evaluated in pediatric patients.

Race: Pharmacokinetic differences due to race have not been studied.

Gender: Studies comparing the pharmacokinetics in different genders had conflicting results. When a single 40 mg trospium chloride dose was administered to 16 elderly subjects, exposure was 45% lower in elderly females compared to elderly males. When 20 mg trospium chloride was dosed twice daily for 4 days to 6 elderly males and 6 elderly females (60 to 75 years), AUC and Cmax were 26% and 68% higher, respectively, in females without hormone replacement therapy than in males.

Renal Impairment: In a clinical pharmacokinetic study where a single dose of 40 mg immediate release trospium chloride was administered to 12 healthy males and 12 males with severe renal impairment, severe renal impairment (creatinine clearance less than 30 mL/minute) significantly altered the disposition of trospium chloride. A 4.2-fold and 1.8-fold increase in mean AUC(0 to ∞) and Cmax, respectively, and the appearance of an additional elimination phase with a long half-life (~33 hours vs. 18 hours) were detected in patients with severe renal impairment compared with nearly age-matched subjects with creatinine clearance equal to or higher than 80 mL/min. The different pharmacokinetic behavior of trospium chloridein patients with severe renal impairment necessitates adjustment of dosage frequency [see Dosage and Administration (2)]. The pharmacokinetics of trospium have not been studied in patients with creatinine clearance ranging from 30 to 80 mL/min.

Hepatic Impairment: In a clinical pharmacokinetic study in patients with mild (Child-Pugh score 5 to 6) and with moderate (Child-Pugh score 7 to 8) hepatic impairment, given a single dose of 40 mg immediate-release trospium chloride, mean Cmax increased 12% and 63%, respectively, and mean AUC(0 to ∞) decreased 5% and 15%, respectively, compared to healthy subjects. There is no information regarding the effect of severe hepatic impairment on exposure to trospium chloride.

13 NONCLINICAL TOXICOLOGY

13.1 Carcinogenesis, Mutagenesis, Impairment of Fertility

Carcinogenesis: Carcinogenicity studies with trospium chloride were conducted in mice and rats for 78 weeks and 104 weeks, respectively, at maximally tolerated doses. No evidence of a carcinogenic effect was found in either mice or rats administered up to 200 mg/kg/day, approximately 9 times the expected clinical exposure levels at the maximum recommended human dose (MRHD) of 40 mg.

Mutagenesis: Trospium chloride was not mutagenic nor genotoxic in tests in vitro in bacteria (Ames test) and mammalian cells (L5178Y mouse lymphoma and CHO cells) or in vivo in the rat micronucleus test.

Impairment of Fertility: No evidence of impaired fertility was observed in rats administered doses up to 200 mg/kg/day (about 16 times the expected clinical exposure at the MRHD, based on AUC).

14 CLINICAL STUDIES

Trospium chloride was evaluated for the treatment of patients with overactive bladder who had symptoms of urinary frequency, urgency, and urge incontinence in two U.S. 12-week, placebo-controlled studies and one 9-month open label extension.

Study 1 was a randomized, double-blind, placebo-controlled, parallel-group study in 523 patients. A total of 262 patients received trospium chloride 20 mg twice daily and 261 patients received placebo. The majority of patients were Caucasian (85%) and female (74%) with a mean age of 61 years (range: 21 to 90 years). Entry criteria required that patients have urge or mixed incontinence (with a predominance of urge), urge incontinence episodes of at least 7 per week, and greater than 70 micturitions per week. The patient’s medical history and urinary diary during the treatment-free baseline confirmed the diagnosis. Reductions in urinary frequency, urge incontinence episodes and urinary void volume for placebo and trospium chloride treatment groups are summarized in Table 3 and Figures 2 and 3.

Table 3. Mean (SE) change from baseline to end of treatment (Week 12 or last observation carried forward) for urinary frequency, urge incontinence episodes, and void volume in Study 1

Efficacy endpoint | Placebo; N=256 | Trospium Chloride; N=253 | P-value
Urinary frequency/24 hoursa,*
Mean baseline | 12.9 | 12.7
Mean change from baseline | -1.3 (0.2) | -2.4 (0.2) | <0.001
Urge incontinence episodes/weekb,*
Mean baseline | 30.1 | 27.3
Mean change from baseline | -13.9 (1.2) | -15.4 (1.1) | 0.012
Urinary void volume/toilet void (mL)a,c
Mean baseline | 156.6 | 155.1
Mean change from baseline | 7.7 (3.1) | 32.1 (3.1) | <0.001
a Treatment differences assessed by analysis of variance for ITT:LOCF data set.
b Treatment differences assessed by ranked analysis of variance for ITT:LOCF data set.
c Placebo N=253, trospium chloride N=248.
* Denotes co-primary endpoint.
ITT=intent-to-treat, LOCF=last observation carried forward.

Figure 2 – Mean Change from Baseline in Urinary Frequency/24 Hours, by Visit: Study 1

Figure 3 – Mean Change from Baseline in Urge Incontinence/Week, by Visit: Study 1

Study 2 was nearly identical in design to Study 1. A total of 329 patients received trospium chloride 20 mg twice daily and 329 patients received placebo. The majority of patients were Caucasian (88%) and female (82%) with a mean age of 61 years (range: 19 to 94 years). Entry criteria were identical to Study 1. Reductions in urinary frequency, urge incontinence episodes, and urinary void volume for placebo and trospium chloride treatment groups are summarized in Table 4 and Figures 4 and 5.

Table 4. Mean (SE) change from baseline to end of treatment (Week 12 or last observation carried forward) for urinary frequency, urge incontinence episodes, and void volume in Study 2

Efficacy endpoint | Placebo; N=325 | Trospium Chloride; N=323 | P-value
Urinary frequency/24 hoursa,*
Mean baseline | 13.2 | 12.9
Mean change from baseline | -1.8 (0.2) | -2.7 (0.2) | <0.001
Urge incontinence episodes/weekb
Mean baseline | 27.3 | 26.9
Mean change from baseline | -12.1 (1) | -16.1 (1) | <0.001
Urinary void volume/toilet void (mL)a,c
Mean baseline | 154.6 | 154.8
Mean change from baseline | 9.4 (2.8) | 35.6 (2.8) | <0.001
a Treatment differences assessed by analysis of variance for ITT: LOCF data set.
b Treatment differences assessed by ranked analysis of variance for ITT: LOCF data set.
c Placebo N=320, trospium chloride N=319.
* Denotes primary endpoint
ITT=intent-to-treat, LOCF=last observation carried forward.

Figure 4 – Mean Change from Baseline in Urinary Frequency/24 Hours, by Visit: Study 2

Figure 5 – Mean Change from Baseline in Urge Incontinence/Week, by Visit: Study 2

16 HOW SUPPLIED/STORAGE AND HANDLING

Trospium Chloride Tablets, USP, 20 mg (brownish yellow, round, biconvex film-coated tablets, debossed with ‘L’ on one side and ‘1’ on the other side) are supplied as follows:

Bottles of 30 NDC 68462-461-30

Bottles of 60 NDC 68462-461-60

Bottles of 500 NDC 68462-461-05

Bottles of 1,000 NDC 68462-461-10

STORAGE AND HANDLING

Store at 20°C to 25°C (68°F to 77°F); excursions permitted to 15°C to 30°C (59°F to 86°F) [see USP Controlled Room Temperature].

17 PATIENT COUNSELING INFORMATION

“See FDA-approved Patient Labeling (Patient Information)”

17.1 Angioedema

Patients should be informed that trospium chloride, the active ingredient in trospium chloride tablets, may produce angioedema which could result in life-threatening airway obstruction. Patients should be advised to promptly discontinue trospium chloride tablets and seek immediate medical attention if they experience edema of the tongue, edema of the laryngopharynx, or difficulty breathing.

17.2 When Not to Use

Prior to treatment, patients should fully understand the risks and benefits of trospium chloride tablets. In particular, patients should be informed not to take trospium chloride tablets if they:

- have urinary retention;
- gastric retention;
- uncontrolled narrow-angle glaucoma;
- are allergic to any component of trospium chloride tablets.

17.3 Administration

Patients should be instructed regarding the recommended dosing and administration of trospium chloride tablets:

- Take one trospium chloride tablet twice daily with water.
- Take trospium chloride tablets on an empty stomach or at least 1 hour before a meal.

17.4 Adverse Reactions

Patients should be informed that the most common side effects with trospium chloride are dry mouth and constipation and that other less common side effects include trouble emptying the bladder, blurred vision, and heat prostration. Because anticholinergics, such as trospium chloride, may produce dizziness or blurred vision, patients should be advised to exercise caution in decisions to engage in potentially dangerous activities until the drug’s effects have been determined. Patients should be informed that alcohol may enhance the drowsiness caused by anticholinergic agents.

Trademarks are the property of their respective owners.

Distributed by:

Glenmark Pharmaceuticals Inc., USA

Elmwood Park, NJ 07407

Questions? 1 (888) 721-7115

www.glenmarkpharma-us.com

August 2025

PATIENT INFORMATION

Trospium Chloride (trose’ pee um klor’ ide) Tablets

Read the Patient Information that comes with trospium chloride tablets before you start taking it and each time you get a refill. There may be new information. This leaflet does not take the place of talking with your doctor about your medical condition or your treatment.

What are trospium chloride tablets?

Trospium chloride tablets are a prescription medicine used to treat adults with overactive bladder who have the following symptoms:

- a strong need to urinate right away;
- leaking or wetting accidents due to a strong need to urinate right away;
- a need to urinate often.

Who should not take trospium chloride tablets?

Do not take trospium chloride tablets if you:

- have trouble emptying your bladder;
- have delayed or slow emptying of your stomach;
- have an eye problem called “uncontrolled narrow-angle glaucoma”;
- are allergic to trospium chloride tablets or any of its ingredients. See the end of this leaflet for a complete list of ingredients.

Trospium chloride tablets have not been studied in children under the age of 18 years.

What should I tell my doctor before starting trospium chloride tablets?

Tell your doctor about all of your medical conditions including if you:

- have any stomach or intestinal problems or problems with constipation;
- have trouble emptying your bladder or have a weak urine stream;
- have an eye problem called narrow-angle glaucoma;
- have kidney problems;
- have liver problems;
- are pregnant or planning to become pregnant. It is not known if trospium chloride tablets can harm your unborn baby.
- are breastfeeding. It is not known if trospium chloride passes into breast milk and if it can harm your baby. You should talk to your doctor about the best way to feed your baby if you are taking trospium chloride tablets.

Tell your doctor about all the medicines you take including prescription and nonprescription medicines, vitamins and herbal supplements. Trospium chloride tablets and certain other medicines can interact and make some side effects worse. Trospium chloride tablets can affect how other medicines are handled by the body.

Know all the medicines you take. Keep a list of them with you to show your doctor and pharmacist each time you get a new medicine.

How should I take trospium chloride tablets?

Take trospium chloride tablets exactly as prescribed.

- Take one trospium chloride tablet twice daily with water.
- Take trospium chloride tablets on an empty stomach or at least 1 hour before a meal.
- If you take too much trospium chloride call your local Poison Control Center or go to an emergency room right away.

What are the possible side effects of trospium chloride tablets?

Trospium chloride tablets may cause allergic reactions that may be serious. Symptoms of a serious allergic reaction may include swelling of the face, lips, throat or tongue. If you experience these symptoms, you should stop taking trospium chloride tablets and get emergency medical help right away.

The most common side effects with trospium chloride tablets are:

- dry mouth;
- constipation;
- headache.

Trospium chloride tablets may cause other less common side effects, including:

- trouble emptying the bladder;
- blurred vision; and drowsiness. Do not drive or operate heavy machinery until you know how trospium chloride tablets affect you. Alcohol can worsen the drowsiness caused by drugs such as trospium chloride tablets.
- heat prostration. Due to decreased sweating, heat prostration can occur when drugs such as trospium chloride tablets are used in a hot environment.

Tell your doctor if you have any side effects that bother you or that do not go away.

These are not all possible side effects of trospium chloride tablets. For more information, ask your doctor, healthcare professional or pharmacist.

How should I store trospium chloride tablets?

- Keep trospium chloride tablets and all other medicines out of the reach of children.
- Store trospium chloride tablets at room temperature, 68°F to 77°F (20°C to 25°C).
- Safely dispose of trospium chloride tablets that are out of date or that you no longer need.

General information about trospium chloride tablets

Medicines are sometimes prescribed for conditions that are not mentioned in patient information leaflets. Do not use trospium chloride tablets for a condition for which they were not prescribed. Do not give trospium chloride tablets to other people, even if they have the same symptoms you have. It may harm them.

This leaflet summarizes the most important information about trospium chloride tablets. If you would like more information, talk with your doctor. You can ask your doctor or pharmacist for information about trospium chloride tablets that is written for health professionals. You can also call Glenmark Pharmaceuticals Inc., USA at 1 (888) 721-7115 or visit www.glenmarkpharma-us.com.

What are the ingredients in trospium chloride tablets?

Active Ingredient: trospium chloride, USP.

Inactive Ingredients: microcrystalline cellulose, lactose monohydrate, corn starch, povidone, croscarmellose sodium, colloidal silicon dioxide, magnesium stearate, titanium dioxide, polyethylene glycol 400, hypromellose, yellow iron oxide and red iron oxide.

Trademarks are the property of their respective owners.

Distributed by:

Glenmark Pharmaceuticals Inc., USA
Elmwood Park, NJ 07407

Questions? 1 (888) 721-7115

www.glenmarkpharma-us.com

Revised: August 2025

PACKAGE/LABEL PRINCIPAL DISPLAY PANEL

NDC 68462-461-60
TROSPIUM CHLORIDE TABLETS USP
20 mg
Pharmacist: Dispense the patient information sheet provided separately to each patient.